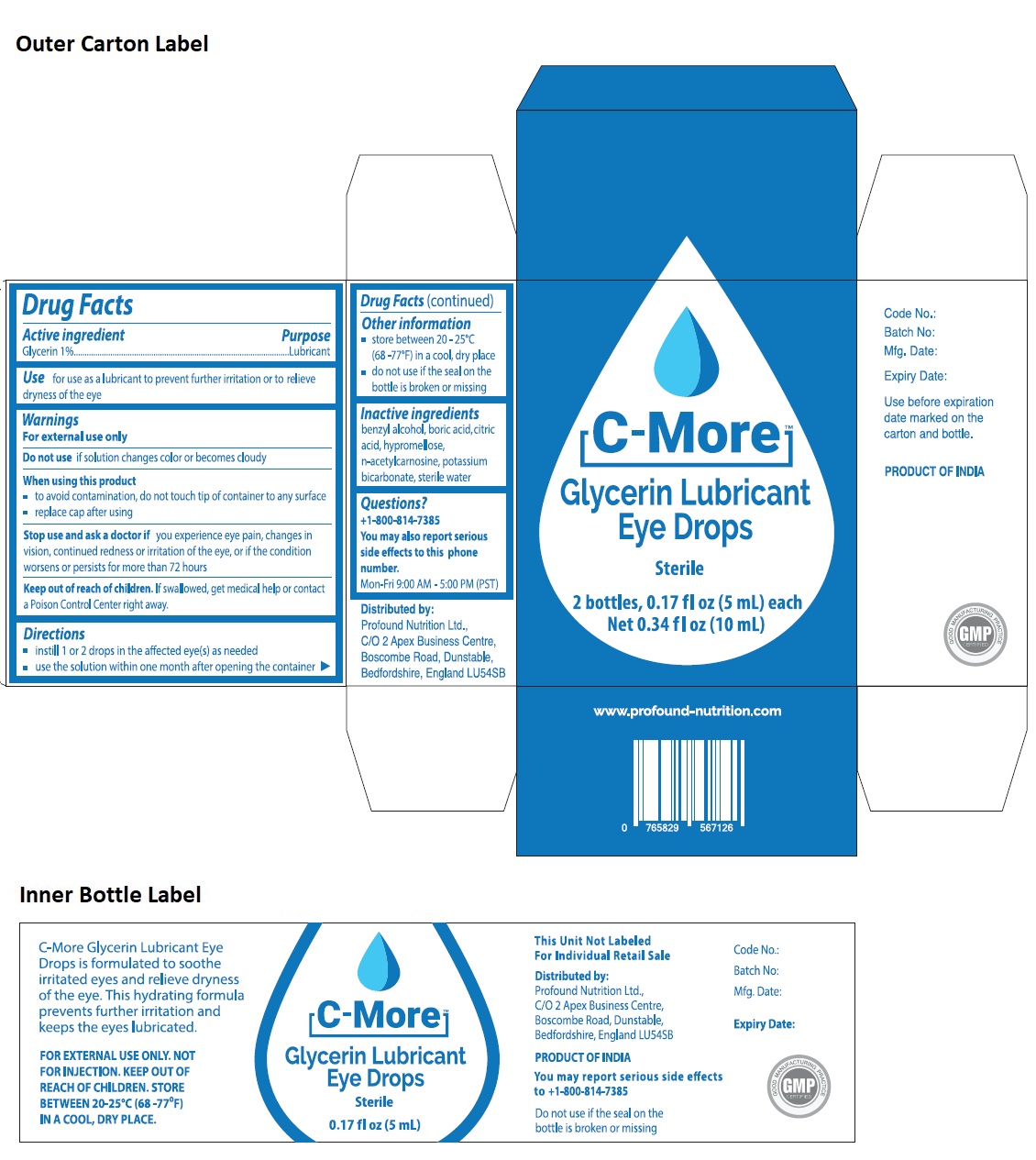 DRUG LABEL: C-MORE Glycerin Lubricant Eye Drops
NDC: 82974-001 | Form: SOLUTION/ DROPS
Manufacturer: PROFOUND NUTRITION LIMITED
Category: otc | Type: HUMAN OTC DRUG LABEL
Date: 20221006

ACTIVE INGREDIENTS: GLYCERIN 13 mg/1 mL
INACTIVE INGREDIENTS: BENZYL ALCOHOL; BORIC ACID; CITRIC ACID MONOHYDRATE; HYPROMELLOSE, UNSPECIFIED; N-ACETYLCARNOSINE; POTASSIUM BICARBONATE; WATER

C-More™ Glycerin Lubricant Eye Drops

Active ingredient

Glycerin 1%

Purpose

Lubricant

Use

for use as a lubricant to prevent further irritation or to relieve dryness of the eye

Warnings

For external use only

Do not use if solution changes color or becomes cloudy

When using this product
• to avoid contamination, do not touch tip of container to any surface
• replace cap after using
Stop use and ask a doctor if you experience eye pain, changes in vision, continued redness or irritation of the eye, or if the condition worsens or persists for more than 72 hours

Keep out of reach of children. If swallowed, get medical help or contact a Poison Control Center right away.

Directions

• instill 1 or 2 drops in the affected eye(s) as needed
• use the solution within one month after opening the container

Other information

• store between 20 - 25°C (68 -77°F) in a cool, dry place
• do not use if the seal on the bottle is broken or missing

Inactive ingredients

benzyl alcohol, boric acid, citric acid, hypromellose, n-acetylcarnosine, potassium bicarbonate, sterile water

Questions?

+1-800-814-7385

You may also report serious side effects to this phone number.

Mon-Fri 9:00 AM - 5:00 PM (PST)

Sterile

C-More Glycerin Lubricant Eye Drops is formulated to soothe irritated eyes and relieve dryness of the eye. This hydrating formula
prevents further irritation and keeps the eyes lubricated.

NOT FOR INJECTION

Distributed by:
Profound Nutrition Ltd.,
C/O 2 Apex Business Centre,
Boscombe Road, Dunstable,
Bedfordshire, England LU54SB

www.profound-nutrition.com

Use before expiration date marked on the carton and bottle.

PRODUCT OF INDIA

Do not use if the seal on the bottle is broken or missing